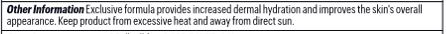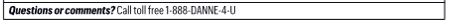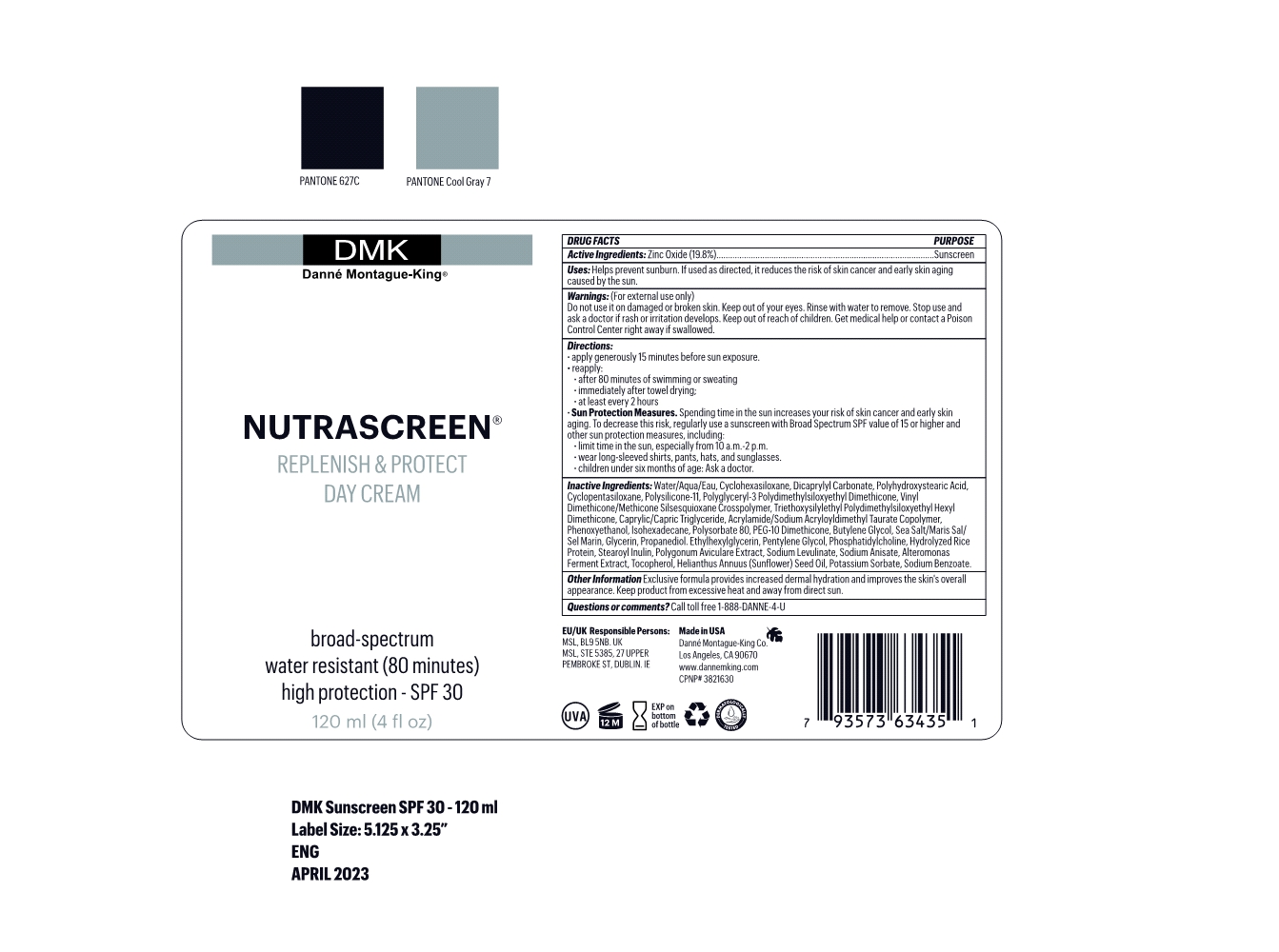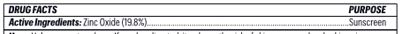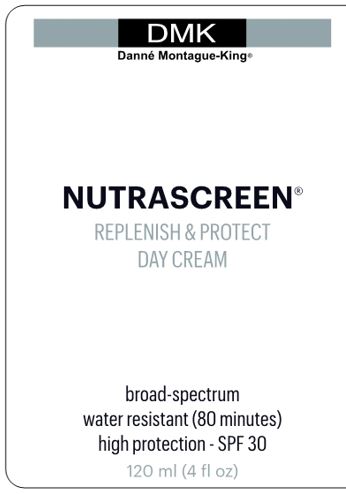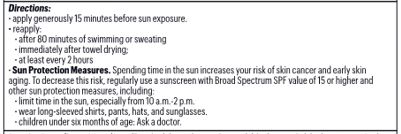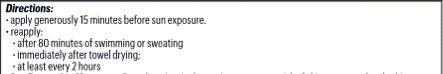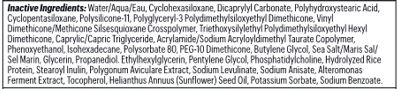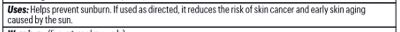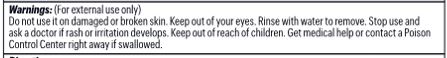 DRUG LABEL: Nutrascreen
NDC: 81537-102 | Form: LOTION
Manufacturer: Danne Montague King
Category: otc | Type: HUMAN OTC DRUG LABEL
Date: 20240719

ACTIVE INGREDIENTS: ZINC OXIDE 19.8 g/100 mL
INACTIVE INGREDIENTS: SUNFLOWER OIL 0.001 g/100 mL; DIMETHICONE/VINYL DIMETHICONE CROSSPOLYMER (SOFT PARTICLE) 3.5 g/100 mL; ALTEROMONAS MACLEODII POLYSACCHARIDES 0.01 g/100 mL; CYCLOMETHICONE 6 11 g/100 mL; CYCLOMETHICONE 5 3.56 g/100 mL; SODIUM ACRYLOYLDIMETHYLTAURATE-ACRYLAMIDE COPOLYMER (1:1; 90000-150000 MPA.S) 1.2 g/100 mL; VINYL DIMETHICONE/METHICONE SILSESQUIOXANE CROSSPOLYMER 2 g/100 mL; TRIETHOXYSILYLETHYL POLYDIMETHYLSILOXYETHYL HEXYL DIMETHICONE 1.7 g/100 mL; PHENOXYETHANOL 1.125 g/100 mL; DICAPRYLYL CARBONATE 8 g/100 mL; POLYHYDROXYSTEARIC ACID (2300 MW) 4 g/100 mL; TOCOPHEROL 0.001 g/100 mL; WATER 38.6705 g/100 mL; SEA SALT 0.2 g/100 mL; ETHYLHEXYLGLYCERIN 0.125 g/100 mL; PHOSPHATIDYLCHOLINE, SOYBEAN 0.07 g/100 mL; ISOHEXADECANE 1 g/100 mL; POLYSORBATE 80 0.8 g/100 mL; PEG-10 DIMETHICONE (600 CST) 0.5 g/100 mL; BUTYLENE GLYCOL 0.24 g/100 mL; STEAROYL INULIN 0.05 g/100 mL; POLYGLYCERYL-3 POLYDIMETHYLSILOXYETHYL DIMETHICONE (4000 MPA.S) 2.38 g/100 mL; MEDIUM-CHAIN TRIGLYCERIDES 1.5 g/100 mL; POTASSIUM SORBATE 0.004 g/100 mL; SODIUM BENZOATE 0.004 g/100 mL; SODIUM LEVULINATE 0.01 g/100 mL; SODIUM ANISATE 0.01 g/100 mL; PROPANEDIOL 0.15 g/100 mL; GLYCERIN 0.172 g/100 mL; PENTYLENE GLYCOL 0.075 g/100 mL; POLYGONUM AVICULARE WHOLE 0.02 g/100 mL

Nutrascreen SPF 30